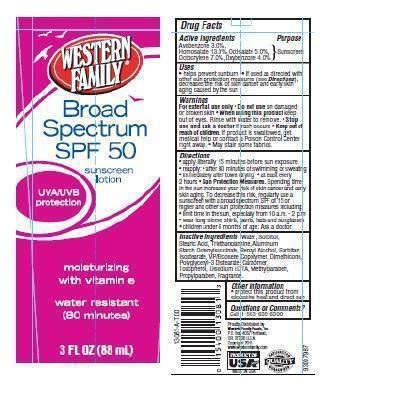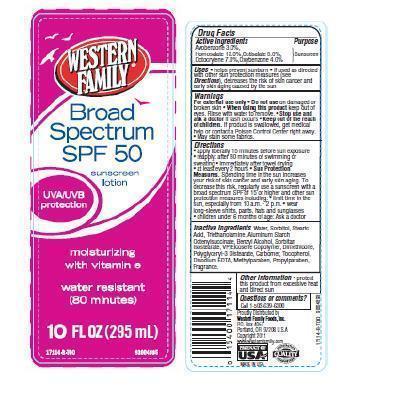 DRUG LABEL: Western Family Broad Spectrum SunscreenSPF 50
          
NDC: 55312-006 | Form: LOTION
Manufacturer: WESTERN FAMILY FOODS, INC.
Category: otc | Type: HUMAN OTC DRUG LABEL
Date: 20140702

ACTIVE INGREDIENTS: AVOBENZONE 3 g/100 g; HOMOSALATE 13 g/100 g; OCTISALATE 5 g/100 g; OCTOCRYLENE 7 g/100 g; OXYBENZONE 4 g/100 g
INACTIVE INGREDIENTS: WATER; SORBITOL; STEARIC ACID; TROLAMINE; ALUMINUM STARCH OCTENYLSUCCINATE; BENZYL ALCOHOL; SORBITAN ISOSTEARATE; DIMETHICONE; METHYLPARABEN; TOCOPHEROL; EDETATE DISODIUM; PROPYLPARABEN; POLYGLYCERYL-3 DISTEARATE

Drug Facts

Active ingredients

Avobenzone 3.0 %

Homosalate 13.0%

Octisalate 5.0%

Octocrylene 7.0%

Oxybenzone 4.0%

Purpose

Sunscreen

Uses

- Helps prevent sunburn
- If used as directed with other sun protection measures (see Directions), decrease the risk of skin cancer and early skin aging caused by the sun

Warnings

For external use only. Do not use on damaged or broken skin.

When using this product

- keep out of eyes. Rinse with water to remove.

Stop use and ask a doctor if

- rash occurs

Keep out of reach of children

If swallowed, get medical help or contact a Poison Control Center right away.

Directions

- apply liberally 15 minutes before sun exposure
- reapply
- after 80 minutes of swimming or sweating
- immediately after towel drying
- at least every 2 hours
- Sun Protection Measures: Spending time in the sun increases your risk of skin cancer and early skin aging. To decrease this risk, regularly use a sunscreen with a broad spectrum SPF of 15 or higher and other sun protection measures including:
- limit time in the sun, especially from 10 a.m. - 2 p.m.
- wear long-sleeve shirts, pants, hats and sunglasses
- children under 6 months of age: Ask a doctor

Other information

- protect this product from excessive heat and direct sun

Inactive ingredients

Water, Sorbitol, Stearic Acid, Triethanolamine, Aluminum Starch Octenylsuccinate, Benzyl Alcohol, Sorbitan Isostearate, VP/Eicosene Copolymer, Dimethicone, Polyglyceryl-3 Distearate, Carbomer, Tocopherol, Disodium EDTA, Methylparaben, Propylparaben, Fragrance.

Principal Display Panel

WESTERN FAMILY

Broad Spectrum SPF 50

sunscreen lotion

UVA/UVB protection

moisturizing with vitamin e

Water Resistant (80 Minutes)

3 FL OZ (88 mL)

WESTERN FAMILY

Broad Spectrum SPF 50

sunscreen lotion

UVA/UVB protection

moisturizing with vitamin e

Water Resistant (80 Minutes)

10 FL OZ (295 mL)

Questions or comments?

Call 1-503-639-6300